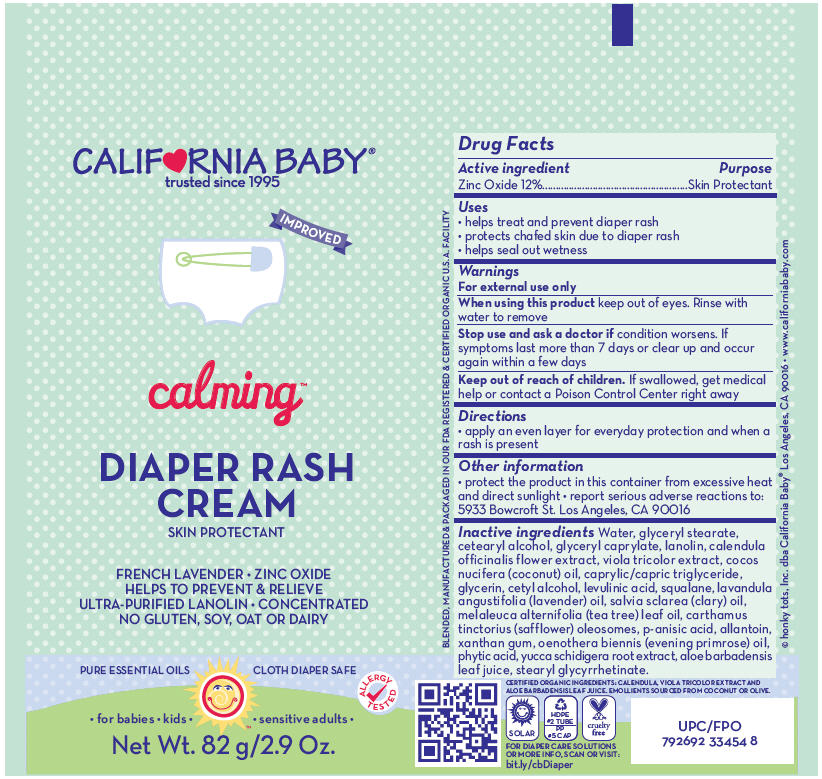 DRUG LABEL: CALMING DIAPER RASH
NDC: 52915-100 | Form: CREAM
Manufacturer: ORGANIC & SUSTAINABLE BEAUTY
Category: otc | Type: HUMAN OTC DRUG LABEL
Date: 20150902

ACTIVE INGREDIENTS: ZINC OXIDE 120 mg/1 g
INACTIVE INGREDIENTS: Water; glyceryl stearate SE; cetostearyl alcohol; glyceryl caprylate; lanolin; calendula officinalis flower; viola tricolor; coconut oil; medium-chain triglycerides; glycerin; cetyl alcohol; levulinic acid; squalane; lavender oil; clary sage oil; tea tree oil; carthamus tinctorius seed oleosomes; p-anisic acid; allantoin; xanthan gum; evening primrose oil; fytic acid; yucca schidigera root; aloe vera leaf; stearyl glycyrrhetinate

CALMING™ DIAPER RASH CREAM

Drug Facts

Active ingredient

Zinc Oxide 12%

Purpose

Skin Protectant

Uses

- helps treat and prevent diaper rash
- protects chafed skin due to diaper rash
- helps seal out wetness

Warnings

For external use only

When using this product keep out of eyes. Rinse with water to remove

Stop use and ask a doctor if condition worsens. If symptoms last more than 7 days or clear up and occur again within a few days

Keep out of reach of children. If swallowed, get medical help or contact a Poison Control Center right away

Directions

- apply an even layer for everyday protection and when a rash is present

Other information

- protect the product in this container from excessive heat and direct sunlight
- report serious adverse reactions to: 5933 Bowcroft St. Los Angeles, CA 90016

Inactive ingredients

Water, glyceryl stearate, cetearyl alcohol, glyceryl caprylate, lanolin, calendula officinalis flower extract, viola tricolor extract, cocos nucifera (coconut) oil, caprylic/capric triglyceride, glycerin, cetyl alcohol, levulinic acid, squalane, lavandula angustifolia (lavender) oil, salvia sclarea (clary) oil, melaleuca alternifolia (tea tree) leaf oil, carthamus tinctorius (safflower) oleosomes, p-anisic acid, allantoin, xanthan gum, oenothera biennis (evening primrose) oil, phytic acid, yucca schidigera root extract, aloe barbadensis leaf juice, stearyl glycyrrhetinate.

PRINCIPAL DISPLAY PANEL - 82 g Tube Label

CALIF♥RNIA BABY®
trusted since 1995

IMPROVED

calming™

DIAPER RASH
CREAM
SKIN PROTECTANT

FRENCH LAVENDER • ZINC OXIDE
HELPS TO PREVENT & RELIEVE
ULTRA-PURIFIED LANOLIN • CONCENTRATED
NO GLUTEN, SOY, OAT OR DAIRY

PURE ESSENTIAL OILS
CLOTH DIAPER SAFE

ALLERGY
TESTED

• for babies • kids •
• sensitive adults •

Net Wt. 82 g/2.9 Oz.